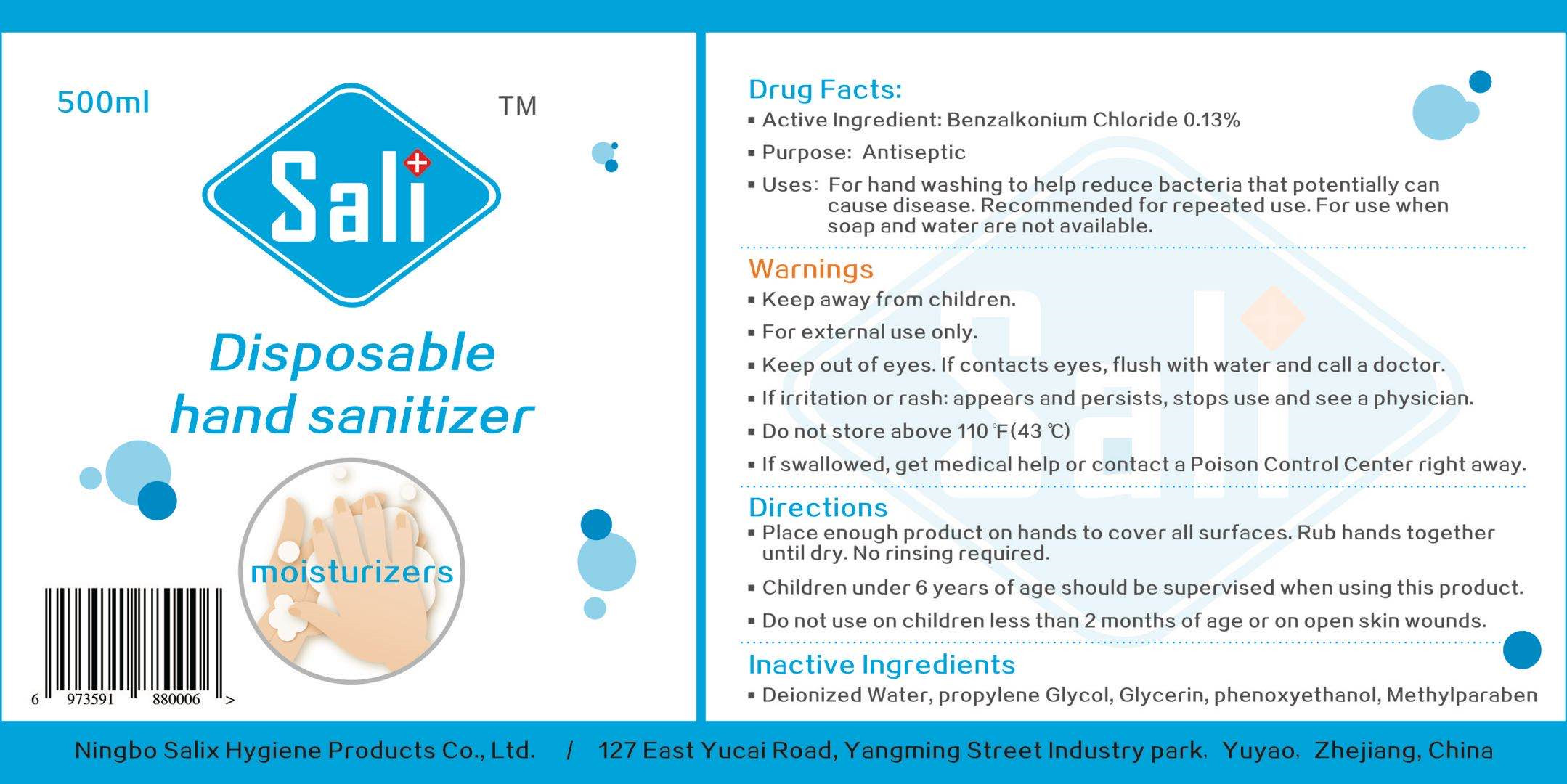 DRUG LABEL: Disposable hand sanitizer
NDC: 55297-001 | Form: SPRAY
Manufacturer: Ningbo Salix Hygiene Products Co., Ltd.
Category: otc | Type: HUMAN OTC DRUG LABEL
Date: 20200806

ACTIVE INGREDIENTS: BENZALKONIUM CHLORIDE 0.65 g/500 mL
INACTIVE INGREDIENTS: WATER; GLYCERIN; METHYLPARABEN; PROPYLENE GLYCOL; PHENOXYETHANOL

DOSAGE AND ADMINISTRATION

Do not store above 110°F(43° C).

INACTIVE INGREDIENT

Deionized Water，Glycerin，Propylene Glycol，Methylparaben, Phenoxyethanol

INDICATIONS AND USAGE

Place enough product on hands to cover all surfaces. Rub hands together until dry. No rinsing required.

ACTIVE INGREDIENT

Benzalkonium Chloride

keep out of reach of children

PURPOSE

Disinfection
Sterilization
No Rinseing

WARNINGS

1.Keep away from children.
2.For external use only.
3.Keep out of eyes. If contacts eyes, flush with water and call a doctor.
4.If irritation or rash: appears and persists, stops use and see a physician.
5.Do not store above 110°F(43° C)
6.If swallowed, get medical help or contact a Poison Control Center right away.